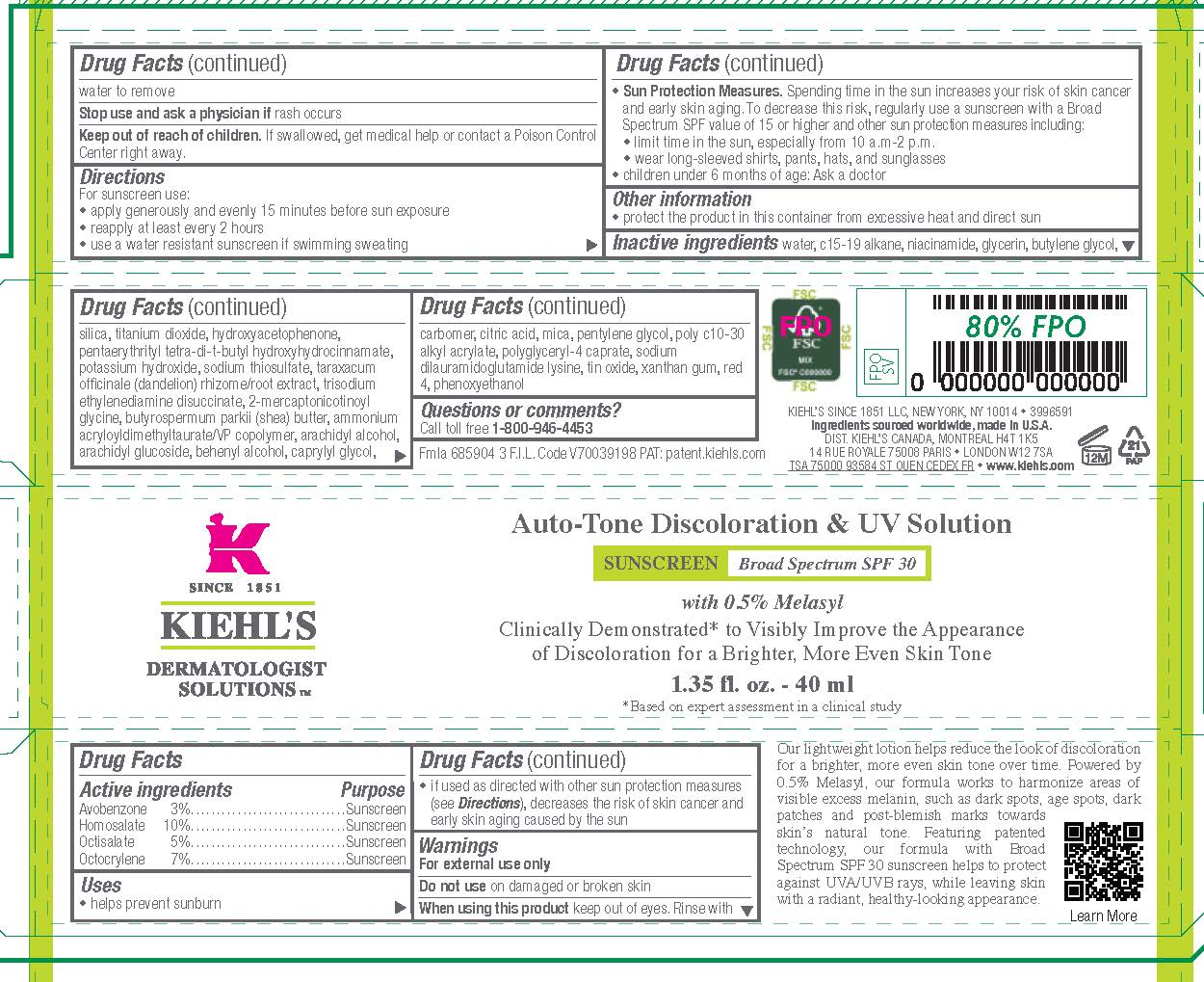 DRUG LABEL: Kiehls Since 1851 Dermatologist Solutions AutoTone Discoloration and UV Solution  Broad Spectrum SPF 30 Sunscreen
NDC: 49967-069 | Form: LOTION
Manufacturer: L'Oreal USA Products Inc
Category: otc | Type: HUMAN OTC DRUG LABEL
Date: 20240627

ACTIVE INGREDIENTS: AVOBENZONE 30 mg/1 mL; HOMOSALATE 100 mg/1 mL; OCTISALATE 50 mg/1 mL; OCTOCRYLENE 70 mg/1 mL
INACTIVE INGREDIENTS: WATER; C15-19 ALKANE; NIACINAMIDE; GLYCERIN; BUTYLENE GLYCOL; SILICON DIOXIDE; TITANIUM DIOXIDE; HYDROXYACETOPHENONE; PENTAERYTHRITOL TETRAKIS(3-(3,5-DI-TERT-BUTYL-4-HYDROXYPHENYL)PROPIONATE); POTASSIUM HYDROXIDE; SODIUM THIOSULFATE; TARAXACUM OFFICINALE ROOT; TRISODIUM ETHYLENEDIAMINE DISUCCINATE; SHEA BUTTER; AMMONIUM ACRYLOYLDIMETHYLTAURATE/VP COPOLYMER; ARACHIDYL ALCOHOL; ARACHIDYL GLUCOSIDE; DOCOSANOL; CAPRYLYL GLYCOL; CARBOMER HOMOPOLYMER, UNSPECIFIED TYPE; CITRIC ACID MONOHYDRATE; MICA; PENTYLENE GLYCOL; BEHENYL ACRYLATE POLYMER; POLYGLYCERYL-4 CAPRATE; SODIUM DILAURAMIDOGLUTAMIDE LYSINE; STANNIC OXIDE; XANTHAN GUM; FD&C RED NO. 4; PHENOXYETHANOL

Drug Facts

Active ingredients

Avobenzone 3%

Homosalate 10%

Octisalate 5%

Octocrylene 7%

Purpose

Sunscreen

Uses

- helps prevent sunburn

- if used as directed with other sun protection measures (see Directions), decreases the risk of skin cancer and early skin aging caused by the sun

Warnings

For external use only

Do not use

on damaged or broken skin

When using this product

keep out of eyes. Rinse with water to remove.

Stop use and ask a doctor if

rash occurs

Keep out of reach of children.

If swallowed, get medical help or contact a Poison Control Center right away.

Directions

For sunscreen use:

● apply liberally 15 minutes before sun exposure

● reapply at least every 2 hours

● use a water resistant sunscreen if swimming or sweating

● Sun Protection Measures. Spending time in the sun increases your risk of skin cancer and early skin aging. To decrease this risk, regularly use a sunscreen with a Broad Spectrum SPF value of 15 or higher and other sun protection measures including:

● limit time in the sun, especially from 10 a.m. – 2 p.m.

● wear long-sleeved shirts, pants, hats, and sunglasses

● children under 6 months of age: Ask a doctor

Other information

protect the product in this container from excessive heat and direct sun

Inactive ingredients

water, C15-19 alkane, niacinamide, glycerin, butylene glycol, silica, titanium dioxide, hydroxyacetophenone, pentaerythrityl tetra-di-t-butyl hydroxyhydrocinnamate, potassium hydroxide, sodium thiosulfate, taraxacum officinale (dandelion) rhizome/root extract, trisodium ethylenediamine disuccinate, 2-mercaptonicotinoyl glycine, butyrospermum parkii (shea) butter, ammonium acryloyldimethyltaurate/VP copolymer, arachidyl alcohol, arachidyl glucoside, behenyl alcohol, caprylyl glycol, carbomer, citric acid, mica, pentylene glycol, poly c10-30 alkyl acrylate, polyglyceryl-4 caprate, sodium dilauramidoglutamide lysine, tin oxide, xanthan gum, red 4, phenoxyethanol

Questions or comments?

Call toll free 1-800-946-4453